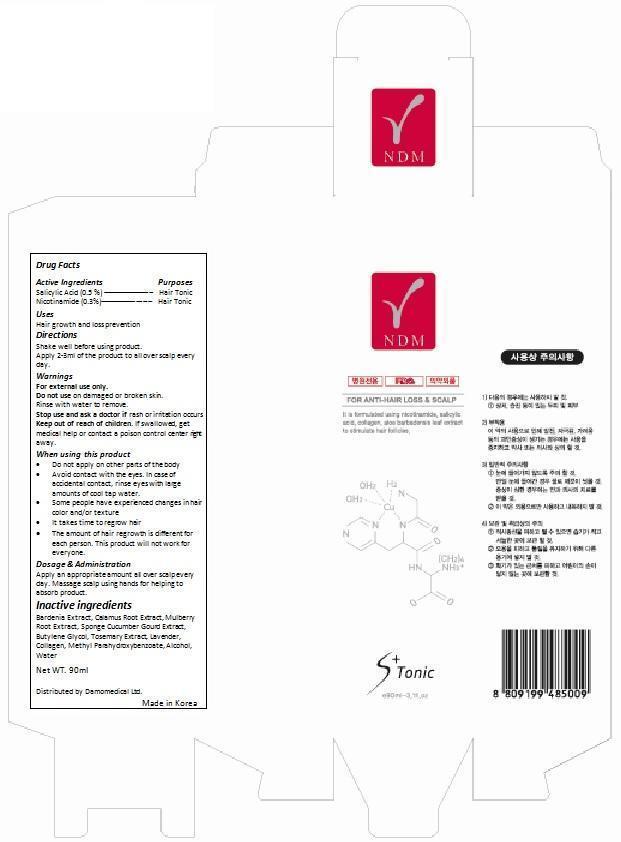 DRUG LABEL: NDM SCALP Tonic
NDC: 69288-002 | Form: LIQUID
Manufacturer: Damomedical Ltd.
Category: otc | Type: HUMAN OTC DRUG LABEL
Date: 20141027

ACTIVE INGREDIENTS: SALICYLIC ACID 0.45 g/90 mL; NIACINAMIDE 0.27 g/90 mL
INACTIVE INGREDIENTS: GARDENIA JASMINOIDES FRUIT; ACORUS CALAMUS ROOT; WHITE MULBERRY; BUTYLENE GLYCOL; ROSEMARY OIL; LAVENDER OIL; METHYLPARABEN; ALCOHOL; WATER

Drug Facts

ACTIVE INGREDIENT

Adenosine (0.04%)

INDICATIONS AND USAGE

Immediately nourishes your skin, resulting in a noticeably brighter, softer, and smother complexion.

WARNINGS

For External Use Only.

DOSAGE AND ADMINISTRATION

Apply one mask sheet at a time.

PURPOSE

Skin Protectant

INSTRUCTIONS FOR USE

After cleansing and applying toner, remove sheet mask from packaging and place carefully around eyes and nose. Relax for 2- minutes. Remove mask and discard.

Keep out of reach of children. If swallowed, get medical help or contact a Poison Control Center right away.

Stop use and ask a doctor if rash occurs.

When using this product keep out of eyes. Rinse with water to remove.

Do not use on damaged or broken skin.

INACTIVE INGREDIENT

Water, Butylene Glycol, Dipropylene Glycol, Glycerin, Alcohol, Trehalose, Lavandula Angustifolia (Lavender) Extract(1%), Diethoxyethyl Succinate, Bis-PEG-18 Methyl Ether Dimethyl Silane, Caprylic/Capric Triglyceride, PEG-60 Hydrogenated Castor Oil, Glyceryl Stearate, Sucrose Polystearate, Cetearyl Glucoside, Hydroxyethyl Acrylate/Sodium Acryloyldimethyl Taurate Copolymer, Carbomer, Phenoxyethanol, Sophora Angustifolia Root Extract, Lonicera Japonica (Honeysuckle) Flower Extract, Camellia Sinensis Leaf Extract, Behenyl Alcohol, Cetearyl Alcohol, Prunus Persica (Peach) Leaf Extract, Ginkgo Biloba Leaf Extract, Potassium Hydroxide, Fragrance, Ethylhexylglycerin, Scutellaria Baicalensis Root Extract, Hydrogenated Lecithin, Glyceryl Polyacrylate, Disodium EDTA, Hydrolyzed Collagen, Caprylyl Glycol, Glyceryl Caprylate, Sodium Hyaluronate